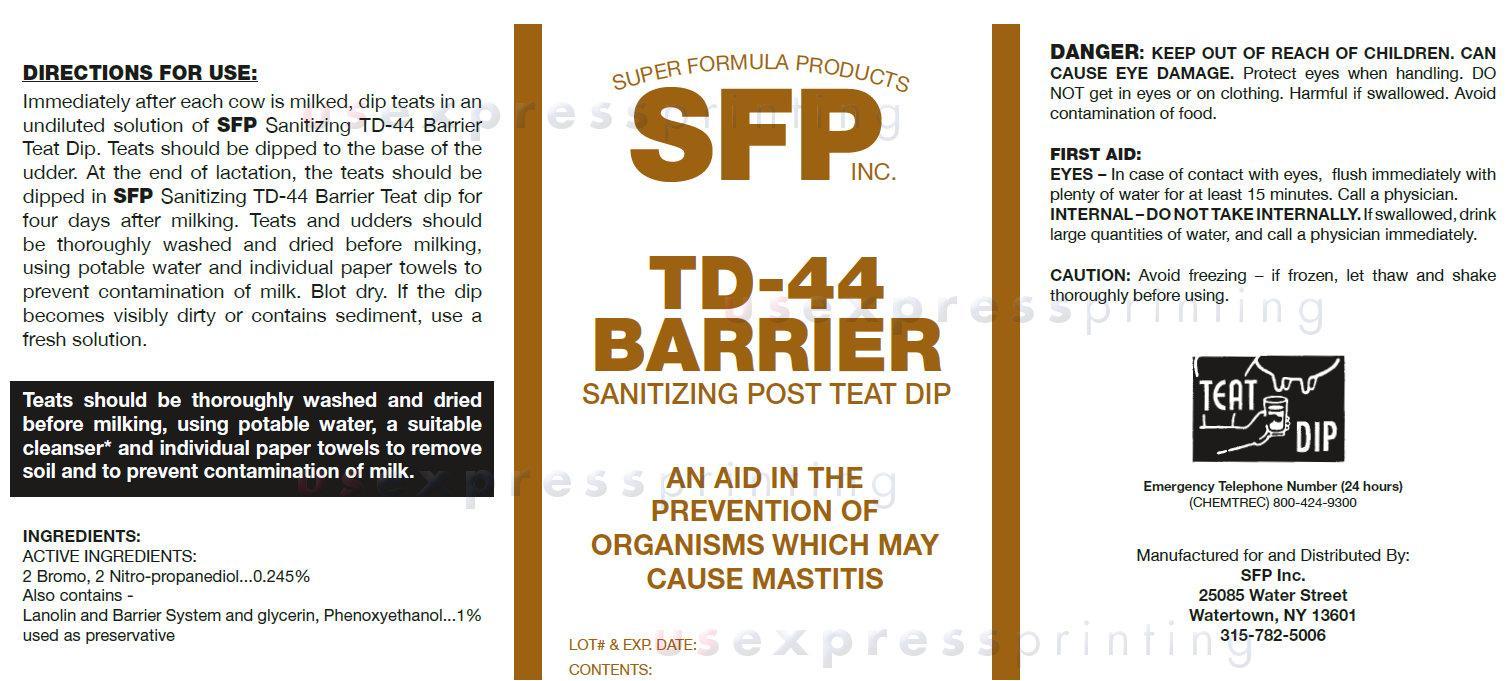 DRUG LABEL: SFP INC. TD-44 BARRIER SANITIZING POST TEAT DIP 
NDC: 35723-102 | Form: LIQUID
Manufacturer: SUPER FORMULA PRODUCTS INC.
Category: animal | Type: OTC ANIMAL DRUG LABEL
Date: 20140723

ACTIVE INGREDIENTS: BRONOPOL 2.45 mg/0.001 L
INACTIVE INGREDIENTS: LANOLIN; GLYCERIN; PHENOXYETHANOL

SFP INC. TD-44 BARRIER SANITIZING POST TEAT DIP

DIRECTIONS FOR USE:

Immediately after each cow is milked, dip teats in an undiluted solution of SFP Sanitizing TD-44 Barrier Teat Dip. Teats should be dipped to the base of the udder. At the end of lactation, the teats should be dipped in SFP Sanitizing TD-44 Barrier Teat dip for four days after milking. Teats and udders should be thoroughly washed and dried before milking, using potable water and individual paper towels to prevent contamination of milk. Blot dry. If the dip becomes visibly dirty or contains sediment, use a fresh solution.
Teats should be thoroughly washed and dried before milking, using potable water, a suitable cleanser* and individual paper towels to remove soil and to prevent contamination of milk.

INGREDIENTS:

ACTIVE INGREDIENTS:
2 Bromo, 2 Nitro-propanediol...0.245%

Also contains -
Lanolin and Barrier System and glycerin, Phenoxyethanol..1% used as preservative

WARNINGS AND PRECAUTIONS

DANGER: Keep Out Of Reach Of Children. Can Cause Eye Damage. Protect eyes when handling. DO NOT get in eyes or on clothing. Harmful if swallowed. Avoid contamination of food.
FIRST AID:
EYES – In case of contact with eyes, flush immediately with plenty of water for at least 15 minutes. Call a physician.
INTERNAL – DO NOT TAKE INTERNALLY. If swallowed, drink large quantities of water, and call a physician immediately.
CAUTION: Avoid freezing – if frozen, let thaw and shake thoroughly before using.